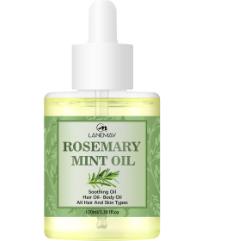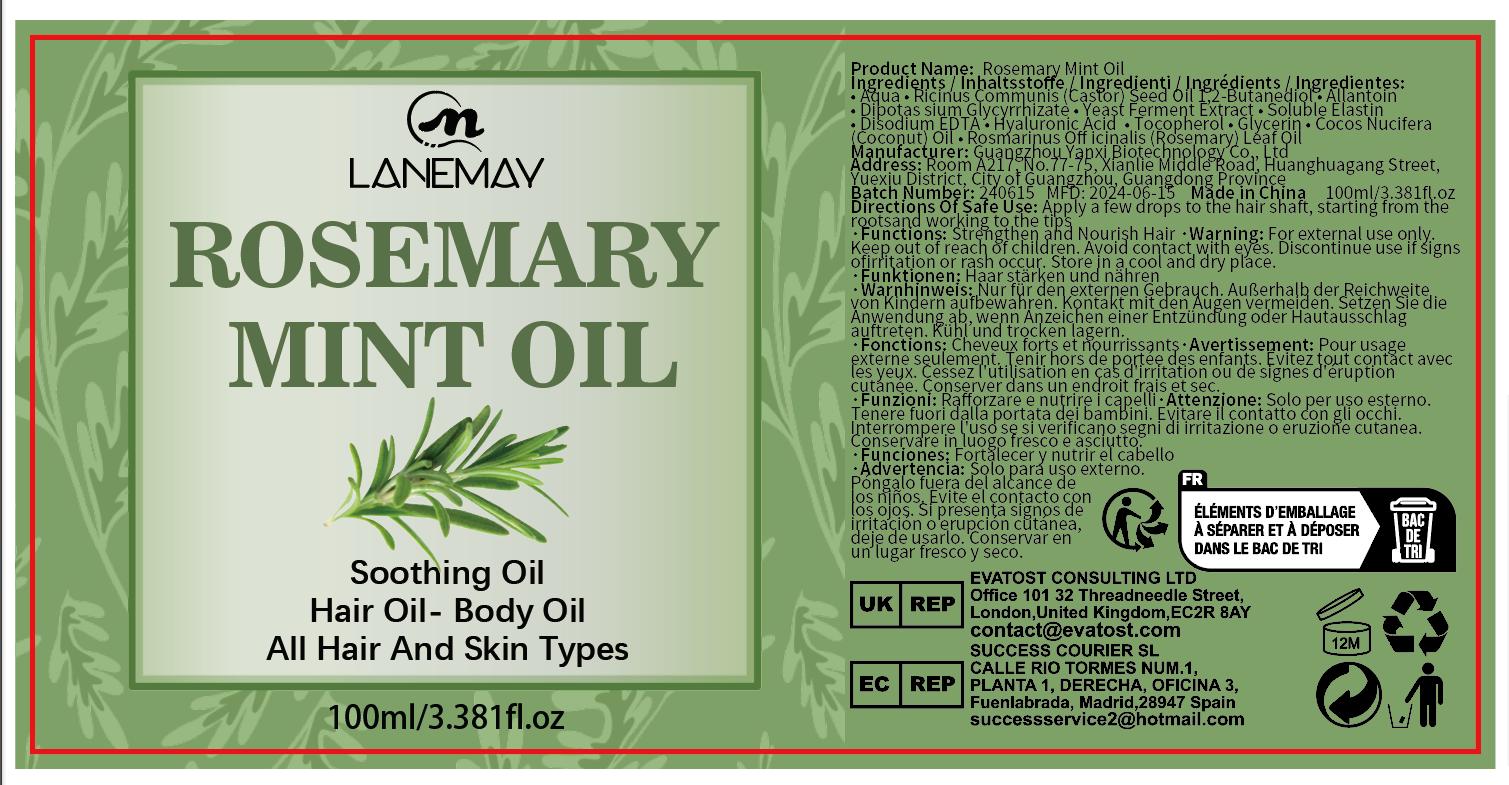 DRUG LABEL: Rosemary Mint Oil
NDC: 84025-055 | Form: CREAM
Manufacturer: Guangzhou Yanxi Biotechnology Co., Ltd
Category: otc | Type: HUMAN OTC DRUG LABEL
Date: 20240710

ACTIVE INGREDIENTS: ALLANTOIN 3 mg/100 mL; HYALURONIC ACID 2 mg/100 mL
INACTIVE INGREDIENTS: WATER

DOSAGE AND ADMINISTRATION

USE AS A NORMAL HAIR CREAM

WARNINGS

keep out of children

INACTIVE INGREDIENT

Aqua

INDICATIONS AND USAGE

For daily hair care

keep out of children

PURPOSE

strong and nourishing hair